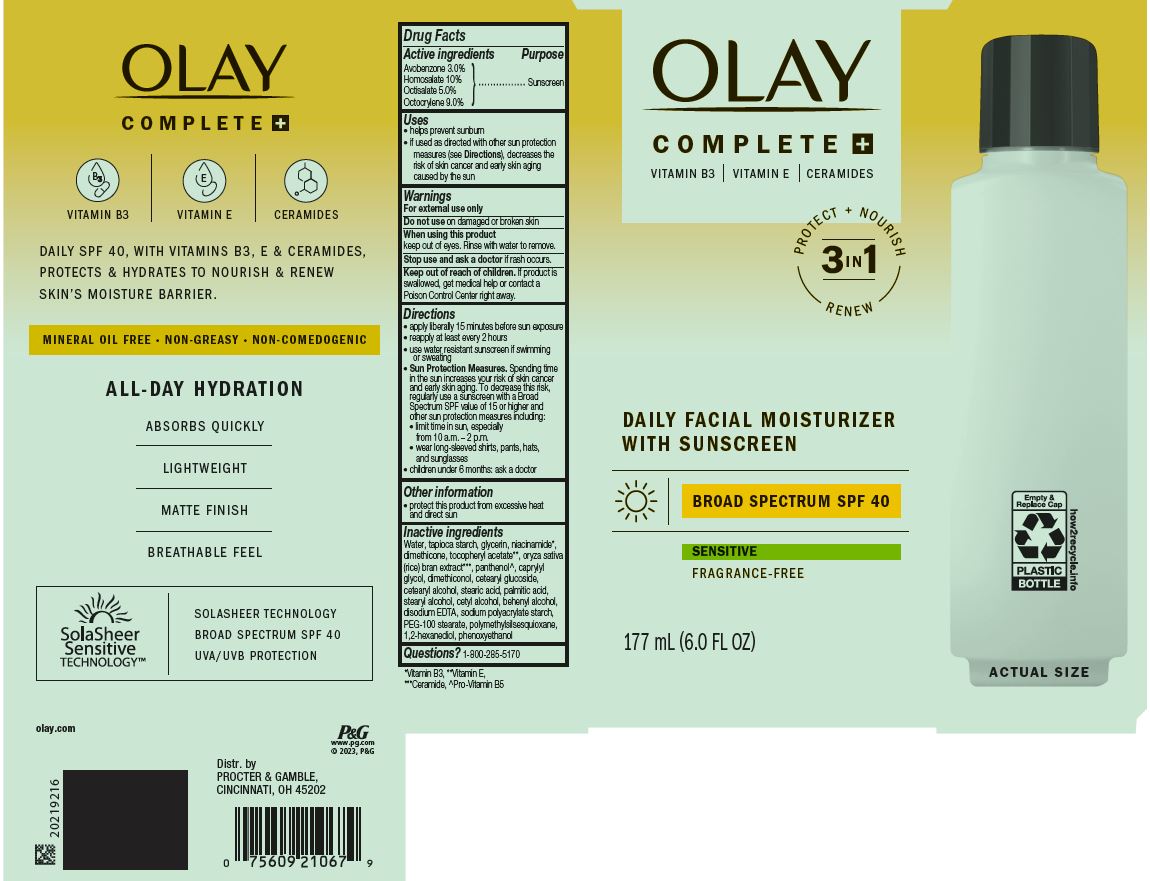 DRUG LABEL: Olay Complete Plus Daily Facial Moisturizer with Sunscreen Broad Spectrum SPF 40
NDC: 84126-032 | Form: LOTION
Manufacturer: The Procter & Gamble Manufacturing Company
Category: otc | Type: HUMAN OTC DRUG LABEL
Date: 20251231

ACTIVE INGREDIENTS: AVOBENZONE 3 g/100 mL; HOMOSALATE 10 g/100 mL; OCTISALATE 5 g/100 mL; OCTOCRYLENE 9 g/100 mL
INACTIVE INGREDIENTS: POLYMETHYLSILSESQUIOXANE (4.5 MICRONS); .ALPHA.-TOCOPHEROL ACETATE; NIACINAMIDE; PHENOXYETHANOL; WATER; GLYCERIN; DIMETHICONE; PANTHENOL; DIMETHICONOL (50000 CST); 1,2-HEXANEDIOL; DOCOSANOL; CETOSTEARYL ALCOHOL; STEARYL ALCOHOL; CETYL ALCOHOL; CETEARYL GLUCOSIDE; STEARIC ACID; PEG-100 STEARATE; EDETATE DISODIUM; STARCH, TAPIOCA; CAPRYLYL GLYCOL; PALMITIC ACID; RICE GERM

Olay ® Complete + Daily Facial Moisturizer with Sunscreen Broad Spectrum SPF 40

Drug Facts

ACTIVE INGREDIENT

Avobenzone 3.0%

Homosalate 10%

Octisalate 5.0%

Octocrylene 9.0%

PURPOSE

Sunscreen

Uses

- helps prevent sunburn
- if used as directed with other sun protection measures (see Directions), decreases the risk of skin cancer and early skin aging caused by the sun

Warnings

For external use only

Do not use on damaged or broken skin

When using this product keep out of eyes. Rinse with water to remove.

Stop use and ask a doctor if rash occurs

Keep out of reach of children. If product is swallowed, get medical help or contact a Poison Control Center right away.

Directions

- apply liberally 15 minutes before sun exposure
- reapply at least every 2 hours
- use water resistant sunscreen if swimming or sweating
- Sun Protection Measures. Spending time in the sun increases your risk of skin cancer and early skin aging. To decrease this risk, regularly use a sunscreen with a Broad Spectrum SPF value of 15 or higher and other sun protection measures including:
  - limit time in sun, especially from 10 a.m. - 2 p.m.
  - wear long-sleeved shirts, pants, hats, and sunglasses
- children under 6 months: ask a doctor

Other information

- protect this product from excessive heat and direct sun

Inactive ingredients

Water, tapioca starch, glycerin, niacinamide, dimethicone, tocopheryl acetate, oryza sativa (rice) bran extract, panthenol, caprylyl glycol, dimethiconol, cetearyl glucoside, cetearyl alcohol, stearic acid, palmitic acid, stearyl alcohol, cetyl alcohol, behenyl alcohol, disodium EDTA, sodium polyacrylate starch, PEG-100 stearate, polymethylsilsesquioxane, 1,2-hexanediol, phenoxyethanol

Questions or comments?

Call 1-800-285-5170

Distr. by PROCTER & GAMBLE,
CINCINNATI, OH 45202

PACKAGE LABEL

OLAY ®

COMPLETE +

DAILY FACIAL MOISTURIZER

WITH SUNSCREEN

BROAD SPECTRUM SPF 40

SENSITIVE

FRAGRANCE-FREE

177 mL (6.0 FL OZ)